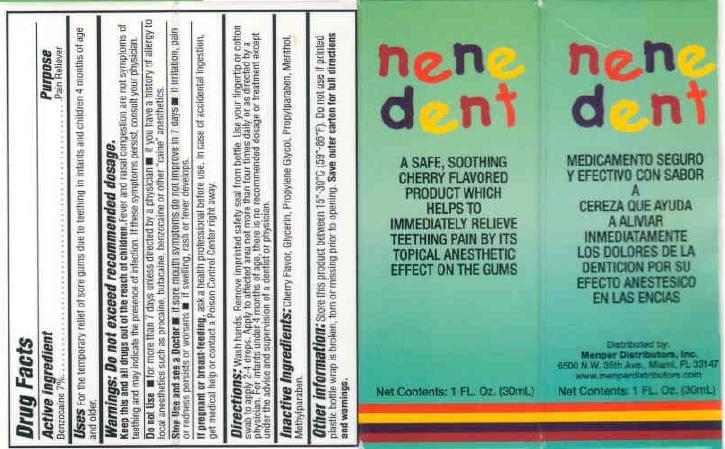 DRUG LABEL: Nene Dente
NDC: 53145-335 | Form: LIQUID
Manufacturer: Menper Distributors, Inc
Category: otc | Type: HUMAN OTC DRUG LABEL
Date: 20150123

ACTIVE INGREDIENTS: BENZOCAINE 2.1 mg/30 mL
INACTIVE INGREDIENTS: GLYCERIN; PROPYLENE GLYCOL; PROPYLPARABEN; MENTHOL; METHYLPARABEN

Active ingredient Purpose

Benzocaine 7%..................................... Pain Reliever

PURPOSE

Pain Reliever

INDICATIONS AND USAGE

Uses For the temporary relief of sore gums due to teething in infants and children 4 months of age and older.

Warnings: Do not exceed recommended dosage.

Keep this and all drugs out of the reach of children. Fever and nasal congestion are not symptoms of teething and may indicate the presence of infection. If these symptoms persist, consult your physician.

Do not Use:

- for more than 7 days unless directed but a physician
- if you have a history of allergy to local anesthetics such as procaine, butacaine, benzocaine, or other "caine" anesthetics

Stop Use and see a Doctor

- if sore mouth symptoms do not improve in 7 days
- if irritation, pain or redness persists or worsens
- if swelling, rash or fever develops

Keep out of reach of children.

PREGNANCY OR BREAST FEEDING

If pregnant or breast-feeding, ask a health professional before use. In case of accidental ingestion, get medical help or contact a Posion Control Center right away.

DOSAGE AND ADMINISTRATION

Directions: wash hands. Remove imprinted safety seal from bottle. Use your fingertip or cotto swab to apply 2-4 drops. Apply to affected area not more than four times daily or as directed by a physician. For infants under 4 months of age, ther is no recommended dosage or treatment execpt under the advice and supervision of a dentist or physician.

Other information: Store this product between 15-30 C (59-86 F). Do not use if printed plastic bottle wrap is broken, toen or missing prior to opening. Save outer carton for full directions and warnings.

INACTIVE INGREDIENT

Inactive ingredients: Cherry flavor, Glycerin, Propylene Glycol, Propylparaben, Menthol, Methylparaben.